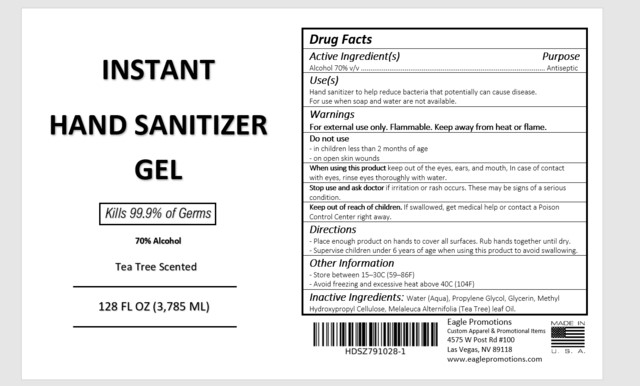 DRUG LABEL: Eagle Promotions
NDC: 73333-128 | Form: GEL
Manufacturer: Nutrix International, LLC.
Category: otc | Type: HUMAN OTC DRUG LABEL
Date: 20200708

ACTIVE INGREDIENTS: ALCOHOL 0.7 g/3974 g
INACTIVE INGREDIENTS: PROPYLENE GLYCOL 0.01 g/3974 g; WATER 0.273 g/3974 g; HYPROMELLOSES 0.007 g/3974 g; TEA TREE OIL 0.002 g/3974 g; GLYCERIN 0.008 g/3974 g

ACTIVE INGREDIENT[S]

Alcohol 70% v/v

PURPOSE

Antiseptic

USE[S]

Hand Sanitizer to help reduce bacteria that potentially can cause disease. For use when soap and water are not available.

WARNINGS

For external use only. Flammable. Keep away from heat or flame.

DO NOT USE

- On children less than 2 months of age. On open skin wounds.

WHEN USING

Keep out of eyes, ears, and mouth. In case of contact with eyes, rinse eyes thoroughly with water.

STOP USE

If irritation or rash occurs. These may be signs of a serious condition.

KEEP OUT OF REACH OF CHILDREN

If swallowed, get medical help, or contact a Poison Control Center right away.

DIRECTIONS

- Place enough product on hands to cover all surfaces. Rub hands together until dry.
- Supervise children under 6 years of age. When using this product avoid swallowing.

OTHER INFORMATION

- Store between 15-30°C (59-86°F) Avoid freezing and excessive heat above 40°C (104°F)

INACTIVE INGREDIENTS

Water (Aqua), Propylene Glycol, Glycerin, Methyl Hydroxypropyl Cellulose, Melaleuca Alternifolia (Tea Tree) Leaf Oil.

DISPLAY PANEL

Label